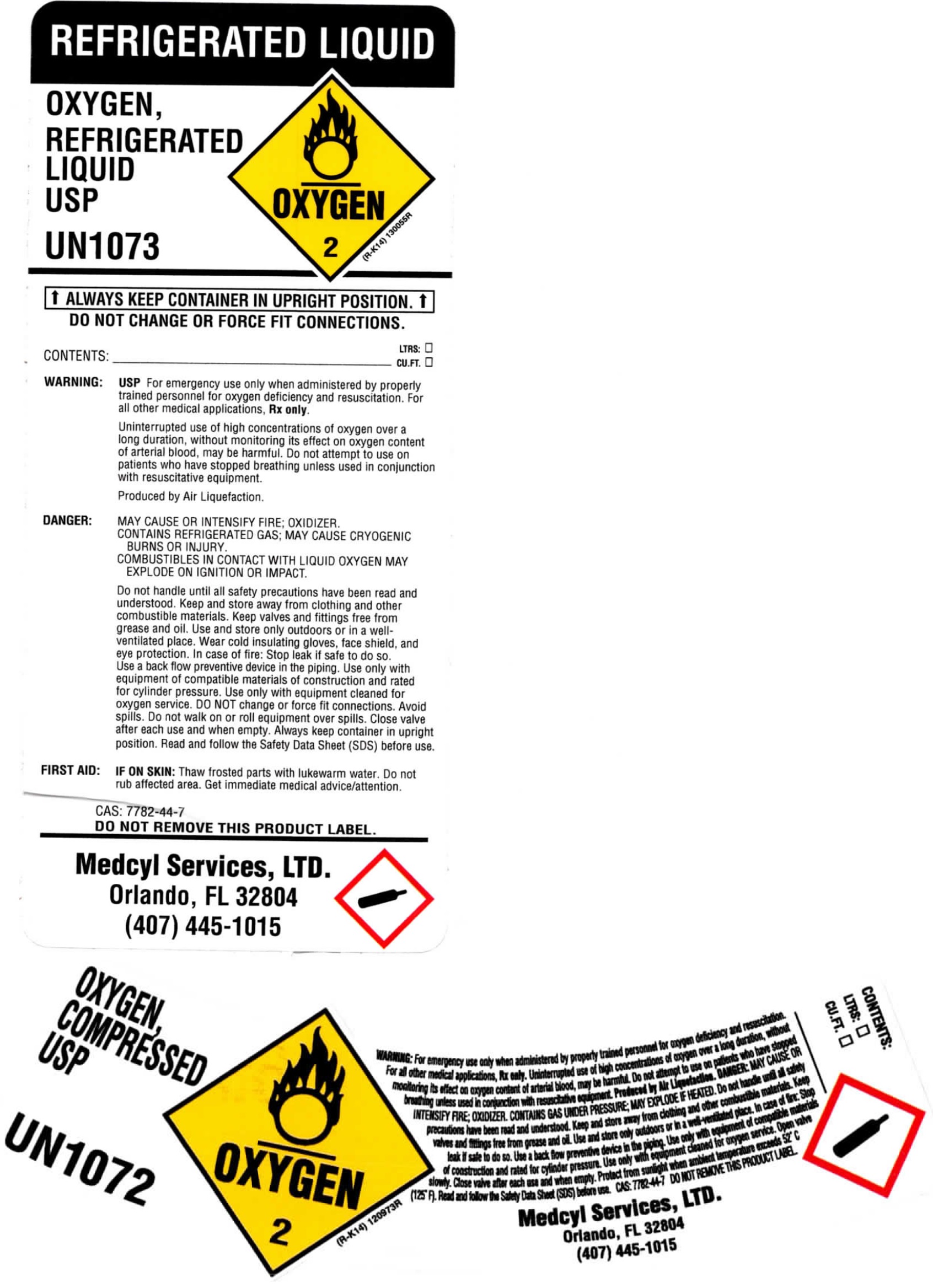 DRUG LABEL: Oxygen Compressed Gas
NDC: 64673-002 | Form: GAS
Manufacturer: MedCyl Services, Ltd.
Category: prescription | Type: HUMAN PRESCRIPTION DRUG LABEL
Date: 20250123

ACTIVE INGREDIENTS: OXYGEN 1 L/1 L

Oxygen, Compressed Gas USP - Size C